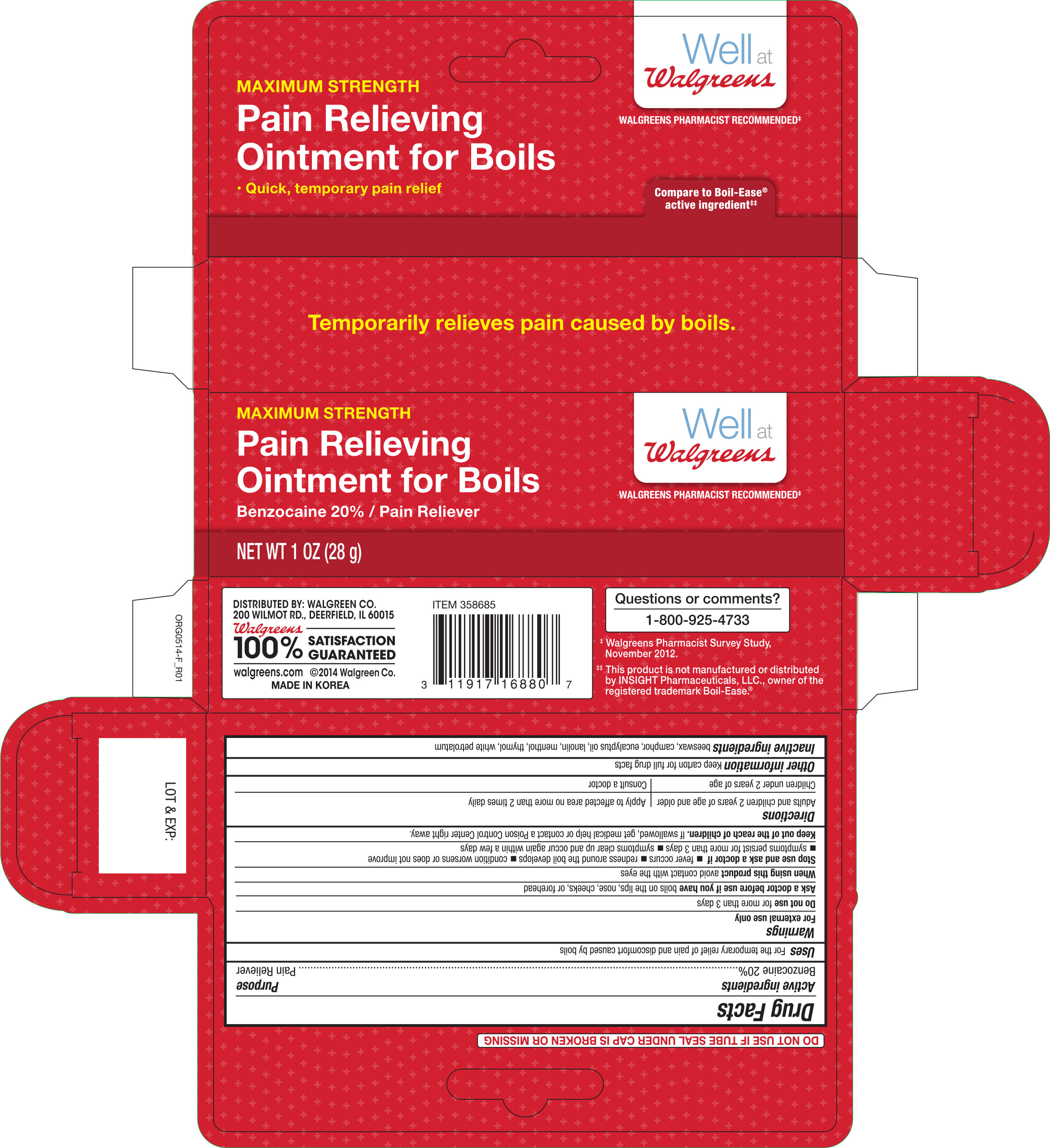 DRUG LABEL: Walgreens Pain Relieving for Boils
NDC: 0363-6880 | Form: OINTMENT
Manufacturer: Walgreen Company
Category: otc | Type: HUMAN OTC DRUG LABEL
Date: 20161012

ACTIVE INGREDIENTS: BENZOCAINE 20 g/100 g
INACTIVE INGREDIENTS: YELLOW WAX; CAMPHOR (SYNTHETIC); EUCALYPTUS OIL; LANOLIN; MENTHOL; THYMOL; PETROLATUM

Active Ingredient Purpose

Benzocaine 20%----------------------------------------------------------- Pain Reliever

Uses

For the temporary relief of pain and discomfort caused by boils

Warnings

For external use only

Do not use for more than 3 days

Ask a doctor before use if you have boils on the lips, nose, cheeks, or forehead

When using this product avoid contact with the eyes

Stop use and ask a doctor if

- fever occurs
- redness around the boil develops
- condition worsens or does not improve
- symptoms persist for more than 3 days
- symptoms clear up and occur again within a few days

KEEP OUT OF REACH OF CHILDREN

Keep out of the reach of children. If swallowed, get medical help or contact a Poison Control Center right away.

Directions

Adults and children 2 years of age and older Apply to affected area no more than 2 times daily

Children under 2 years of age Consult a doctor

Other information

Keep carton for full drug facts

INACTIVE INGREDIENT

Inactive ingredients beeswax, camphor, eucalyptus oil, lanolin, menthol, thymol, white petrolatum

DOSAGE AND ADMINISTRATION

Distributed by:

Walgreen Co.

200 Wilmot Rd.

Deerfield, IL 60015 USA

Made in Korea